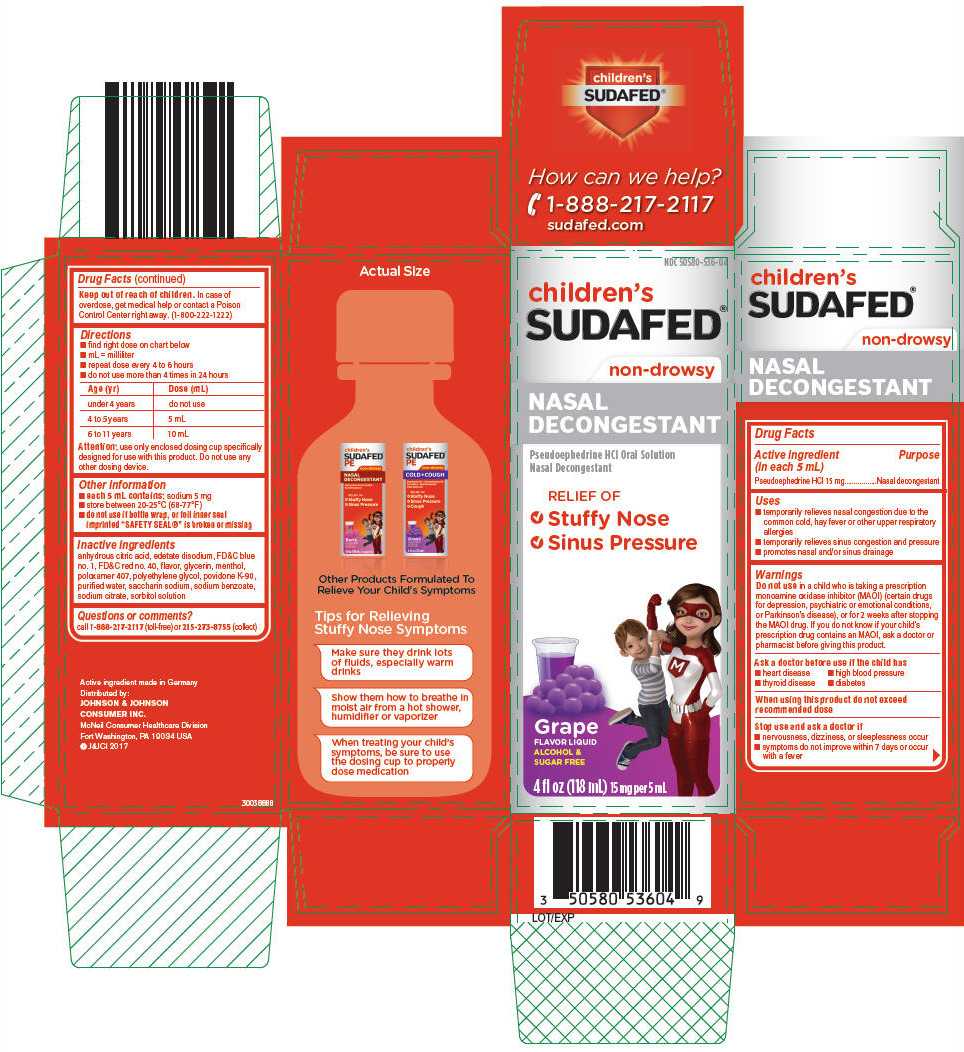 DRUG LABEL: Childrens Sudafed
NDC: 50580-536 | Form: SOLUTION
Manufacturer: Kenvue Brands LLC
Category: otc | Type: HUMAN OTC DRUG LABEL
Date: 20241108

ACTIVE INGREDIENTS: PSEUDOEPHEDRINE HYDROCHLORIDE 15 mg/5 mL
INACTIVE INGREDIENTS: EDETATE DISODIUM; FD&C BLUE NO. 1; FD&C RED NO. 40; GLYCERIN; MENTHOL, UNSPECIFIED FORM; POLOXAMER 407; POLYETHYLENE GLYCOL, UNSPECIFIED; POVIDONE K90; WATER; SACCHARIN SODIUM; SODIUM BENZOATE; SODIUM CITRATE, UNSPECIFIED FORM; SORBITOL SOLUTION; ANHYDROUS CITRIC ACID

Children's Sudafed
Nasal Decongestant

Drug Facts

Active ingredient (in each 5 mL)

Pseudoephedrine HCl 15 mg

Purpose

Nasal decongestant

Uses

- temporarily relieves nasal congestion due to the common cold, hay fever or other upper respiratory allergies
- temporarily relieves sinus congestion and pressure
- promotes nasal and/or sinus drainage

Warnings

Do not use in a child who is taking a prescription monoamine oxidase inhibitor (MAOI) (certain drugs for depression, psychiatric or emotional conditions, or Parkinson's disease), or for 2 weeks after stopping the MAOI drug. If you do not know if your child's prescription drug contains an MAOI, ask a doctor or pharmacist before giving this product.

Ask a doctor before use if the child has

- heart disease
- high blood pressure
- thyroid disease
- diabetes

When using this product do not exceed recommended dose

Stop use and ask a doctor if

- nervousness, dizziness, or sleeplessness occur
- symptoms do not improve within 7 days or occur with a fever

Keep out of reach of children. In case of overdose, get medical help or contact a Poison Control Center right away. (1-800-222-1222)

Directions

- find right dose on chart below
- mL = milliliter
- repeat dose every 4 to 6 hours
- do not use more than 4 times in 24 hours

Age (yr) | Dose (mL)
under 4 years | do not use
4 to 5 years | 5 mL
6 to 11 years | 10 mL

Attention: use only enclosed dosing cup specifically designed for use with this product. Do not use any other dosing device.

Other information

- each 5 mL contains: sodium 5 mg
- store between 20-25°C (68-77°F)
- do not use if bottle wrap, or foil inner seal imprinted "SAFETY SEAL®" is broken or missing

Inactive ingredients

anhydrous citric acid, edetate disodium, FD&C blue no. 1, FD&C red no. 40, flavor, glycerin, menthol, poloxamer 407, polyethylene glycol, povidone K-90, purified water, saccharin sodium, sodium benzoate, sodium citrate, sorbitol solution

Questions or comments?

call 1-888-217-2117 (toll-free) or 215-273-8755 (collect)

PRINCIPAL DISPLAY PANEL

NDC 50580-536-04

children's
SUDAFED®

non-drowsy

NASAL
DECONGESTANT

Pseudoephedrine HCl Oral Solution
Nasal Decongestant

RELIEF OF

- Stuffy Nose
- Sinus Pressure

Grape
FLAVOR LIQUID
ALCOHOL &
SUGAR FREE

4 fl oz (118 mL) 15 mg per 5 mL